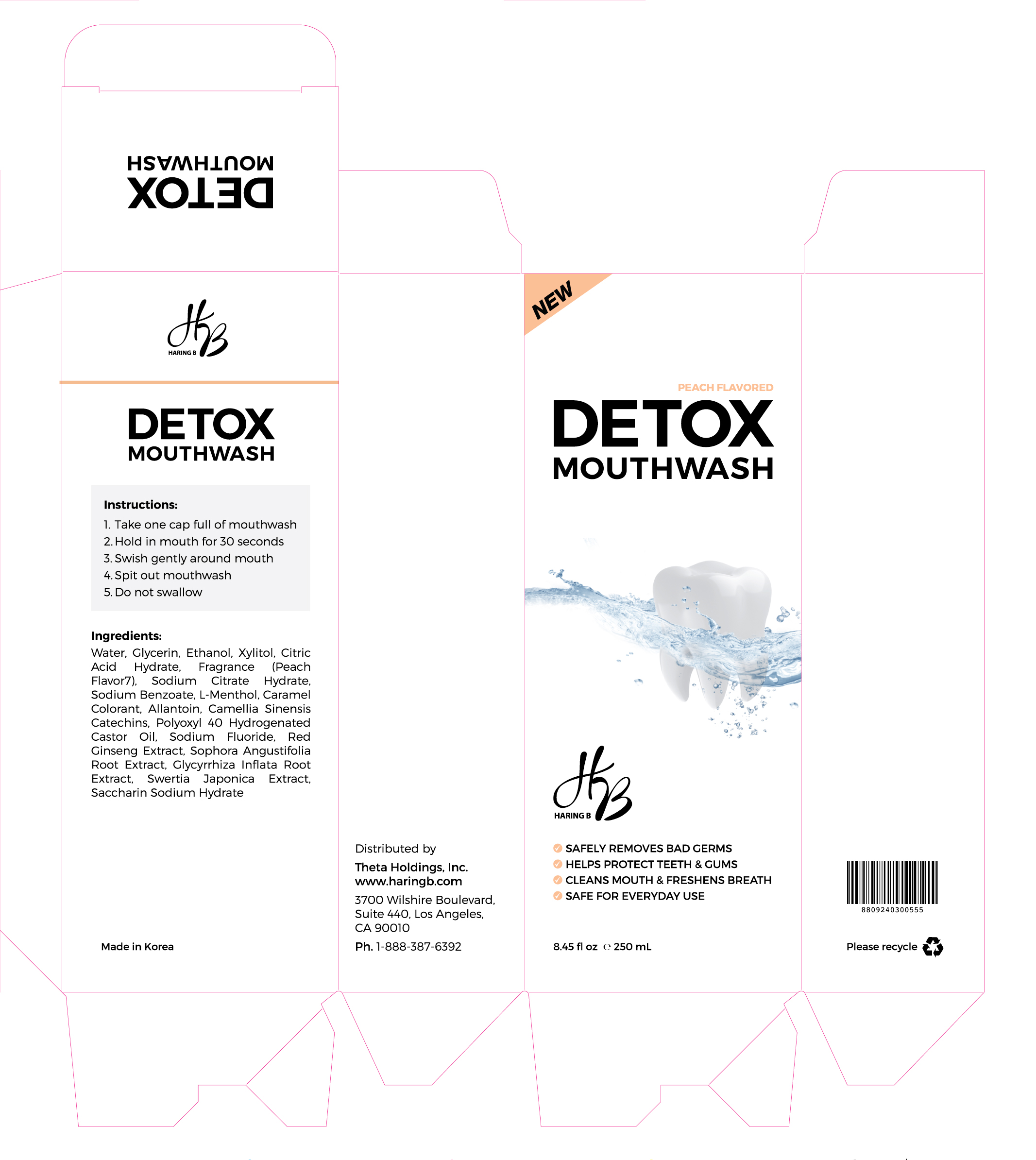 DRUG LABEL: Haring B Detox Mouthwash
NDC: 69255-400 | Form: LIQUID
Manufacturer: JANGIN PHARM CO.,LTD.
Category: otc | Type: HUMAN OTC DRUG LABEL
Date: 20190110

ACTIVE INGREDIENTS: SODIUM FLUORIDE 0.02 g/100 mL
INACTIVE INGREDIENTS: XYLITOL; LEVOMENTHOL; ALLANTOIN

Active ingredient : Sodium fluoride

INACTIVE INGREDIENT

Preservative : Sodium Benzoate

Additives : Allantoin, Glycerin, Ethyl alcohol, Xylitol, Citric Acid Hydrate, Sodium Citrate Hydrate, Caramel Colorant, Glycyrrhiza Inflata Root Extract, Sophora Angustifolia Root Extract, Swertia Japonica Extract, camellia sinensis catechins, Red Ginseng Extract, Saccharin Sodium Hydrate, Polyoxyl 40 Hydrogenated Castor Oil, L-Menthol, Fragrance(Peach Flavor 7), DI-Water

PURPOSE

It keeps your teeth white, strong, and clean your mouth. It makes your mouth feel fresh, prevent cavities, and remove bad breath. Increase the aesthetic effect. Prevent gingivitis, periodontitis (pyorrhoea alveolaris), periodontal disease, and gum disease.

Keep out of reach of children

INDICATIONS AND USAGE

● Administration and doses : Hold a suitable amount (10~15ml) in your mouth for about 30 seconds, then spit it out, and brush your teeth with a brush.

WARNINGS

● Caution : 1) The fluoride content of toothpaste is 90.5 ppm. 2) Take care not to swallow, and rinse your mouth thoroughly after use. 3) If gum or mouth damage is caused by using this toothpaste, stop using it and consult a doctor or dentist. 4) If used by children under the age of six years, use small amount of toothpaste about the size of peas at a time. Use under supervision of a guardian to avoid sucking or swallowing. 5) If a child under 6 years old swallows a large amount, consult a physician or dentist immediately. 6) Keep out of the reach of children under 6 years old. 7) This medicine contains sodium benzoate which can cause slight irritation to the skin, eyes and mucous membrane. 8) This product contains fluoride and ethanol and requires guidance from parents or adults when used by children. 9) This product contains ethanol(alcohol), so be careful when testing ethanol(alcohol) immediately after use as this product may affect the results of drinking measurement.

DOSAGE AND ADMINISTRATION

For dental use only